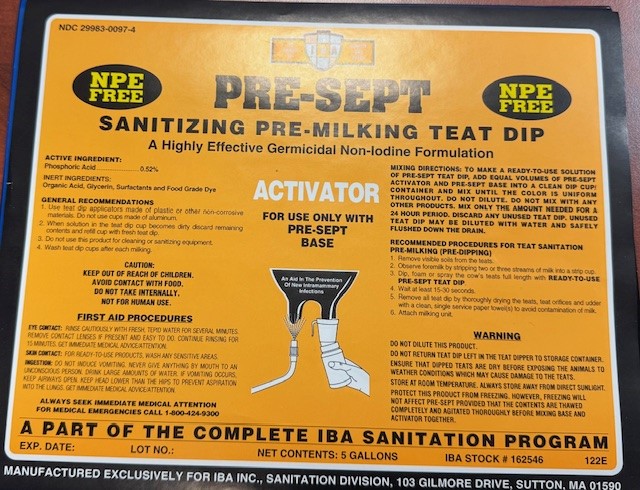 DRUG LABEL: PRE-SEPT ACTIVATOR
NDC: 29983-0097 | Form: SOLUTION
Manufacturer: IBA
Category: animal | Type: OTC ANIMAL DRUG LABEL
Date: 20241226

ACTIVE INGREDIENTS: PHOSPHORIC ACID 5.2 g/1 L
INACTIVE INGREDIENTS: CITRIC ACID; UREA

PRE-SEPT SANITIZING PRE-MILKING TEAT DIP A HIGHLY EFFECTIVE GERMICIDAL NON-IODINE FOMRULATION

ACTIVE INGREDIENT

PHOSPHORIC ACID...........0.52%

INERT INGREDIENTS
Organic Acid, Glycerin, Surfactants and Food Grade Dye

INDICATIONS AND USAGE

GENERAL RECOMMENDATIONS

To make a Ready-to-Use solution of Pre-Sept teat dip, add equal volumes of Pre-Sept Activator and Pre-Sept Base into a clean dip cup/container and mix until the color is uniform throughout. Do not dilute. Do not mix with any other products. Mix only the amount needed for a 24 hour period. Discard any unused teat dip. Unused teat dip may be diluted with water and safely flushed down the drain.

RECOMMENDED PROCEDURES FOR TEAT SANITATION
A. PRE-MILKING (PRE-DIPPING)
1. REMOVE VISIBLE SOILS FROM THE TEATS.
2. OBSERVE FOREMILK BY STRIPPING TWO OR THREE STREAMS OF MILK INTO A STRIP CUP.
3. DIP OR SPRAY THE COW'S TEATS FULL LENGTH WITH READY-TO-USE PRE-SEPT TEAT DIPPLUS TEAT DIP.
4 WAIT APPROXIMATELY 30 SECONDS.
5. REMOVE ALL TEAT DIP BY THOROUGHLY DRYING THE TEATS AND TEAT ORIFICES AND UDDER (IF SPRAYING), WITH A CLEAN, SINGLE SERVICE PAPER TOWEL(S).
6. ATTACH MILKING UNIT

WARNING

Do not dilute this product.
Do not return teat dip left in the teat dipper to storage container.
Ensure that dipped teats are dry before exposing the animals to weather conditions which may cause damage to the teats.
Store at room temperature. Always store away from direct sunlight.
Protect this product from freezing. However, freezing will not affect Pre-Sept provided that the contents are thawed completely and agitated thoroughly before mixing base and activator together

CAUTION: KEEP OUT OF REACH OF CHILDREN.
AVOID CONTACT WITH FOOD. DO NOT TAKE INTERNALLY.

FIRST AID PROCEDURES

EYE CONTACT: Rinse cautiously with fresh, tepid water for several minutes. Remove contact lenses if present and easy to do. Continue rinsing for 15 minutes. Get immediate medical advice/attention. SKIN CONTACT: For RTU products wash any sensitive areas. INGESTION: Do not induce vomiting. Never give anything by mouth to an unconscious person. Drink large amounts of water. If vomiting occurs, keep airways open. Keep head lower than the hips to prevent aspiration into the lungs. Get immediate medical advice/attention.

ALWAYS SEEK IMMEDIATE MEDICAL ATTENTION

FOR MEDICAL EMERGENCIES CALL 1-800-424-9300